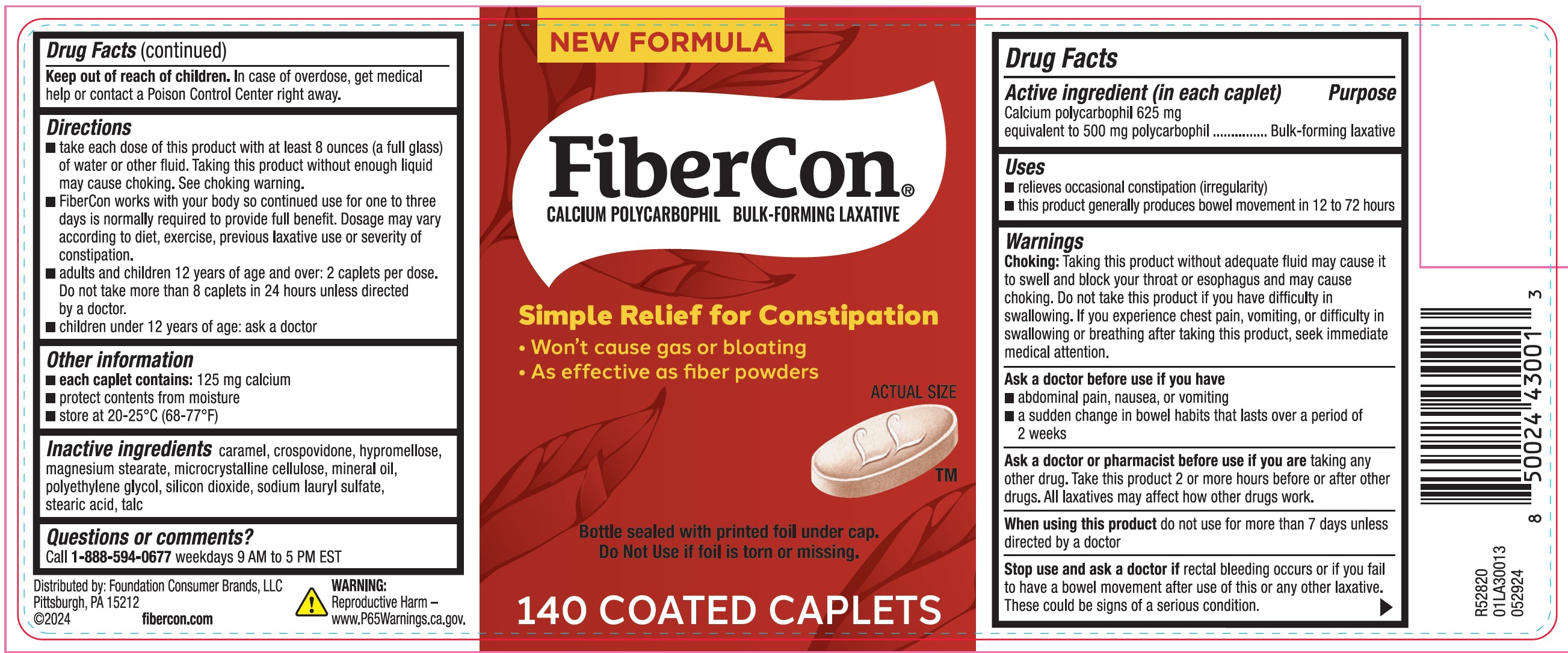 DRUG LABEL: Fibercon
NDC: 80070-500 | Form: TABLET
Manufacturer: Foundation Consumer Brands
Category: otc | Type: HUMAN OTC DRUG LABEL
Date: 20251024

ACTIVE INGREDIENTS: CALCIUM POLYCARBOPHIL 625 mg/1 1
INACTIVE INGREDIENTS: TALC; CARAMEL; MICROCRYSTALLINE CELLULOSE; CROSPOVIDONE (120 .MU.M); HYPROMELLOSE, UNSPECIFIED; MAGNESIUM STEARATE; POLYETHYLENE GLYCOL, UNSPECIFIED; SILICON DIOXIDE; SODIUM LAURYL SULFATE; STEARIC ACID; MINERAL OIL

Fibercon®

Drug Facts

Active ingredient (in each caplet)

Calcium polycarbophil 625 mg equivalent to 500 mg polycarbophil

Purpose

Bulk-forming laxative

Uses

- relieves occasional constipation (irregularity)
- this product generally produces bowel movement in 12 to 72 hours

Warnings

Choking

Taking this product without adequate fluid may cause it to swell and block your throat or esophagus and may cause choking. Do not take this product if you have difficulty in swallowing. If you experience chest pain, vomiting, or difficulty in swallowing or breathing after taking this product, seek immediate medical attention.

Ask a doctor before use if you have

- abdominal pain, nausea, or vomiting
- a sudden change in bowel habits that lasts over a period of 2 weeks

Ask a doctor or pharmacist before use if you aretaking any other drug. Take this product 2 or more hours before or after other drugs. All laxatives may affect how other drugs work.

WHEN USING

When using this productdo not use for more than 7 days unless directed by a doctor

Stop use and ask a doctor ifrectal bleeding occurs or if you fail to have a bowel movement after use of this or any other laxative. These could be signs of a serious condition.

Keep out of reach of children.In case of overdose, get medical help or contact a Poison Control Center right away.

Directions

- take each dose of this product with at least 8 ounces (a full glass) of water or other fluid. Taking this product without enough liquid may cause choking. See chokingwarning.
- FiberCon works naturally so continued use for one to three days is normally required to provide full benefit. Dosage may vary according to diet, exercise, previous laxative use or severity of constipation.
- adults and children 12 years of age and over: 2 caplets per dose. Do not take more than 8 caplets in 24 hours unless directed by a doctor.
- children under 12 years of age: ask a doctor

Other information

- each caplet contains:140 mg calcium and 10 mg magnesium
- protect contents from moisture
- store at 20-25°C (68-77°F)

Inactive ingredients

caramel, crospovidone, hypromellose, magnesium stearate, microcrystalline cellulose, mineral oil, polyethylene glycol, silicon dioxide, sodium lauryl sulfate, stearic acid, talc

Questions or comments?

Call 1-888-594-0677weekdays 9 AM to 5 PM EST

Distributed by: Foundation Consumer Brands, LLC
Pittsburgh, PA 15212

WARNING: Reproductive Harm - www.P65warnings.ca.gov

PRINCIPAL DISPLAY PANEL - 140 Caplet Bottle

NEW FORMULA

FiberCon®

Calcium Polycarbophil
Bulk-Forming Laxative

Simple Relief for Constipation

- Won't cause gas or bloating
- As effective as fiber powders

140 Coated Caplets